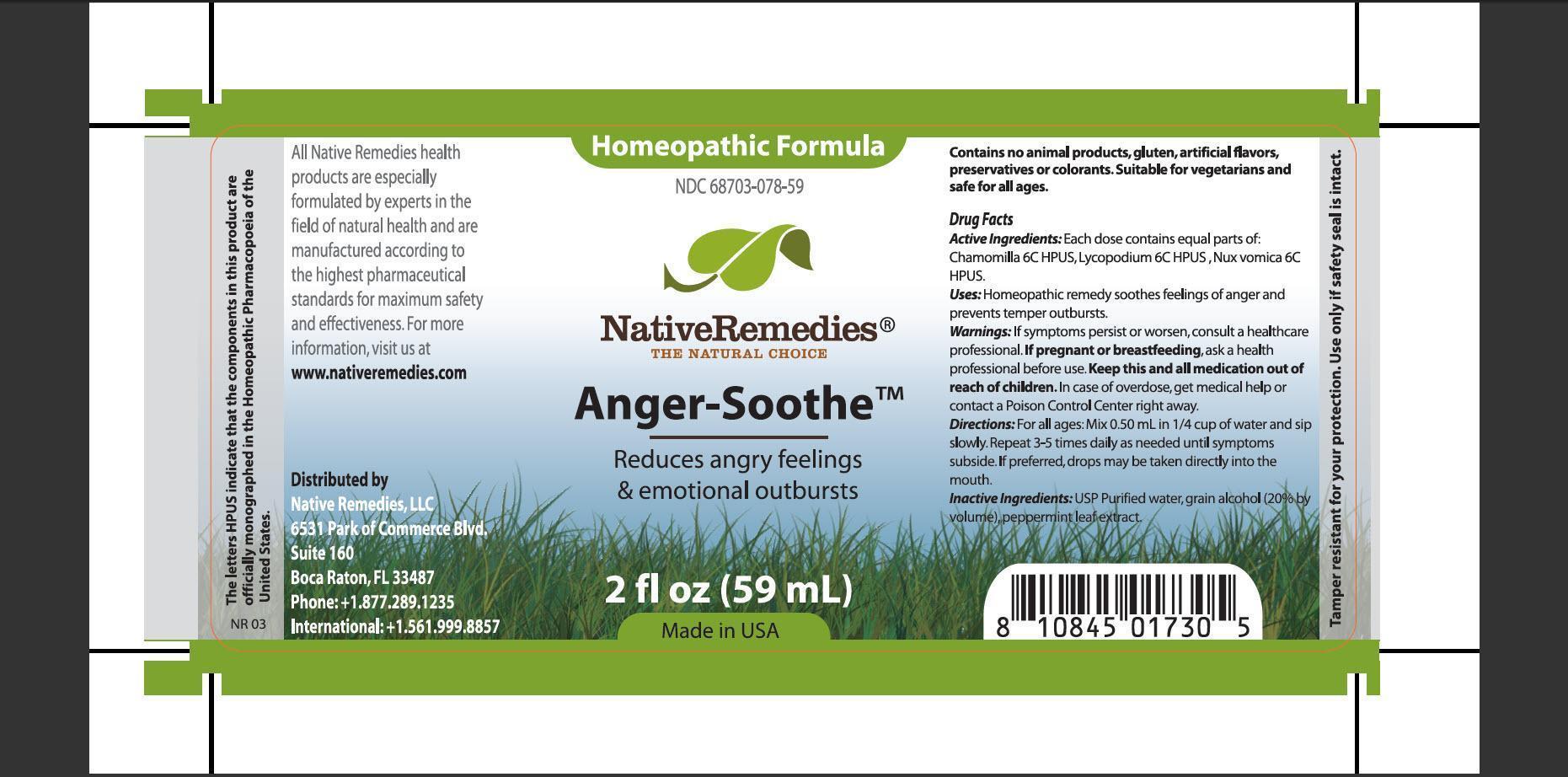 DRUG LABEL: Anger Soothe
NDC: 68703-078 | Form: TINCTURE
Manufacturer: Native Remedies, LLC
Category: homeopathic | Type: HUMAN OTC DRUG LABEL
Date: 20130404

ACTIVE INGREDIENTS: MATRICARIA RECUTITA 6 [hp_C]/1 mL; LYCOPODIUM CLAVATUM SPORE 6 [hp_C]/1 mL; STRYCHNOS NUX-VOMICA SEED 6 [hp_C]/1 mL
INACTIVE INGREDIENTS: WATER; ALCOHOL; Menthol

Anger Soothe

PURPOSE

Reduces angry feeling and emotional outbursts

ACTIVE INGREDIENT

Active Ingredients: Each dose contains equal parts of: Chamomilla 6C HPUS, Lycopodium 6C HPUS, Nux vomica 6C HPUS

INDICATIONS AND USAGE

Uses: Homeopathic remedy soothes feelings of anger and prevents temper outbursts

WARNINGS

Warnings: If symptoms persist or worsen, consult a healthcare professional before use

PREGNANCY OR BREAST FEEDING

If pregnant or breastfeeding, ask a health professional before use

KEEP OUT OF REACH OF CHILDREN

Keep this and all medication out of reach of children

OVERDOSAGE

In case of overdose, get medical help or contact Poison Control Center right away

DOSAGE AND ADMINISTRATION

Directions: For all ages: Mix 0.50 mL in 1/4 cup of water and sip slowly. Repeat 3-5 times daily as needed until symptoms subside. If preferred, drops may be taken directly into the mouth

INACTIVE INGREDIENT

Inactive Ingredients: USP Purified water, grain alcohol (20% by volume), peppermint leaf extract

PATIENT COUNSELING INFORMATION

The letters HPUS indicate that the component in this product are officially monographed in the Homeopathic Pharmacopoeia of the United States

All Native Remedies health products are especially formulated by experts in the field of natural health and are manufactured according to the highest pharmaceutical standards for maximum safety and effectiveness. For more information, visit us at www.nativeremedies.com

Distributed by
Native Remedies, LLC
6531 Park of Commerce Blvd.
Suite 160
Boca Raton, FL 33487
Phone:+1.877.289.1235
International: +1.561.999.8857

Contains no animal products, gluten, artificial flavors, preservatives or colorants. Suitable for vegetarians and safe for all ages